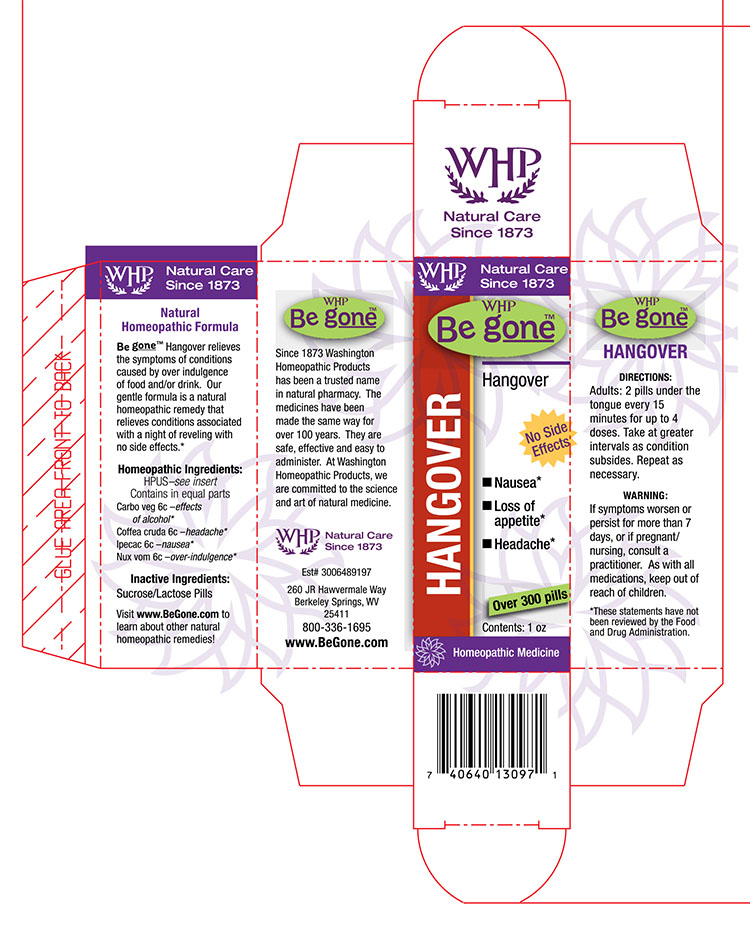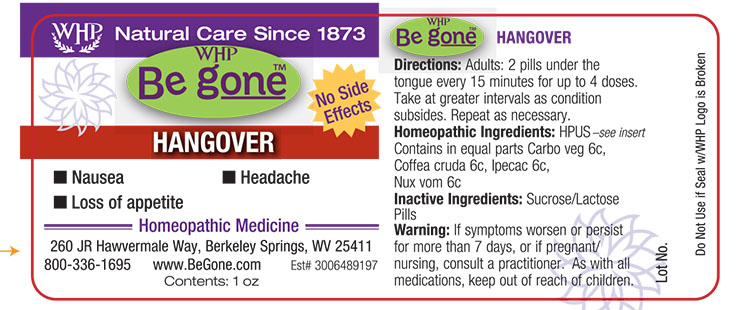 DRUG LABEL: WHP Be gone Hangover
NDC: 68428-997 | Form: PELLET
Manufacturer: Washington Homeopathic Products
Category: homeopathic | Type: HUMAN OTC DRUG LABEL
Date: 20160513

ACTIVE INGREDIENTS: ACTIVATED CHARCOAL 6 [hp_C]/1 1; ARABICA COFFEE BEAN 6 [hp_C]/1 1; IPECAC 6 [hp_C]/1 1; STRYCHNOS NUX-VOMICA SEED 6 [hp_C]/1 1
INACTIVE INGREDIENTS: SUCROSE; LACTOSE

DRUG FACTS

ACTIVE INGREDIENTS

CARBO VEG

COFFEA CRUDA

IPECAC

NUX VOM

USES

Relieves the symptoms of conditions caused by over indulgence of food and/or drink.

KEEP OUT OF REACH OF CHILDREN

As wtih all medications, keep out of reach of children.

INDICATIONS

Carbo veg 6c –effects of alcohol*

Coffea cruda 6c –headache*

Ipecac 6c –nausea*

Nux vom 6c –over-indulgence*

■ Nausea* ■ Loss of appetite* ■ Headache*

*These statements have not been reviewed by the Food and Drug Administration.

STOP USE AND ASK DOCTOR

If symptoms persist or recur, discontinue use. If pregnant or nursing a baby, consult a licensed practitioner before using this product.

DIRECTIONS

Adults: 2 pills every 3 hours for 2 days. Then 2 pills morning and night for 2 weeks.

Children: 1 pill. Repeat as necessary.

INACTIVE INGREDIENTS

Sucrose/Lactose Pills